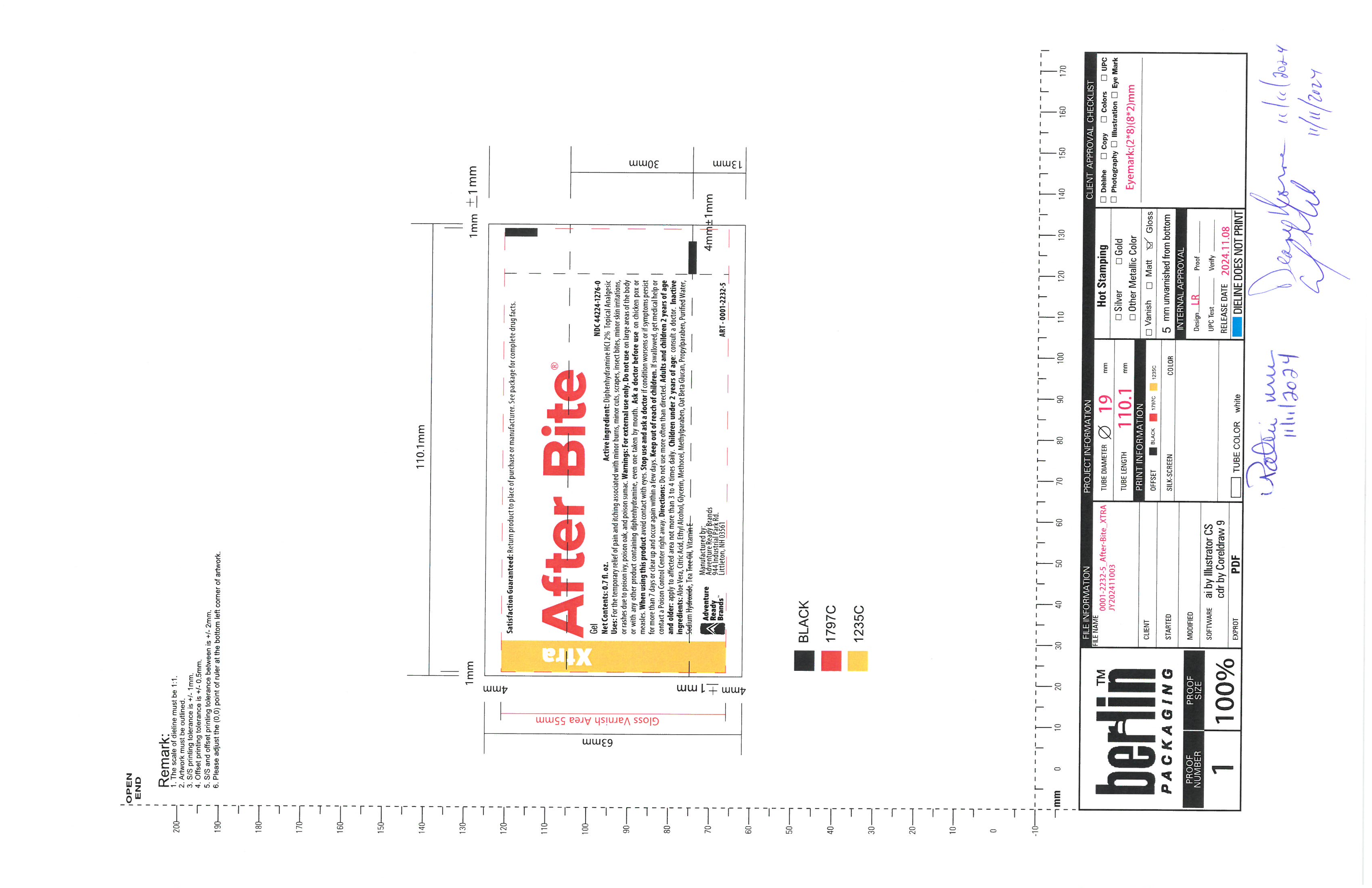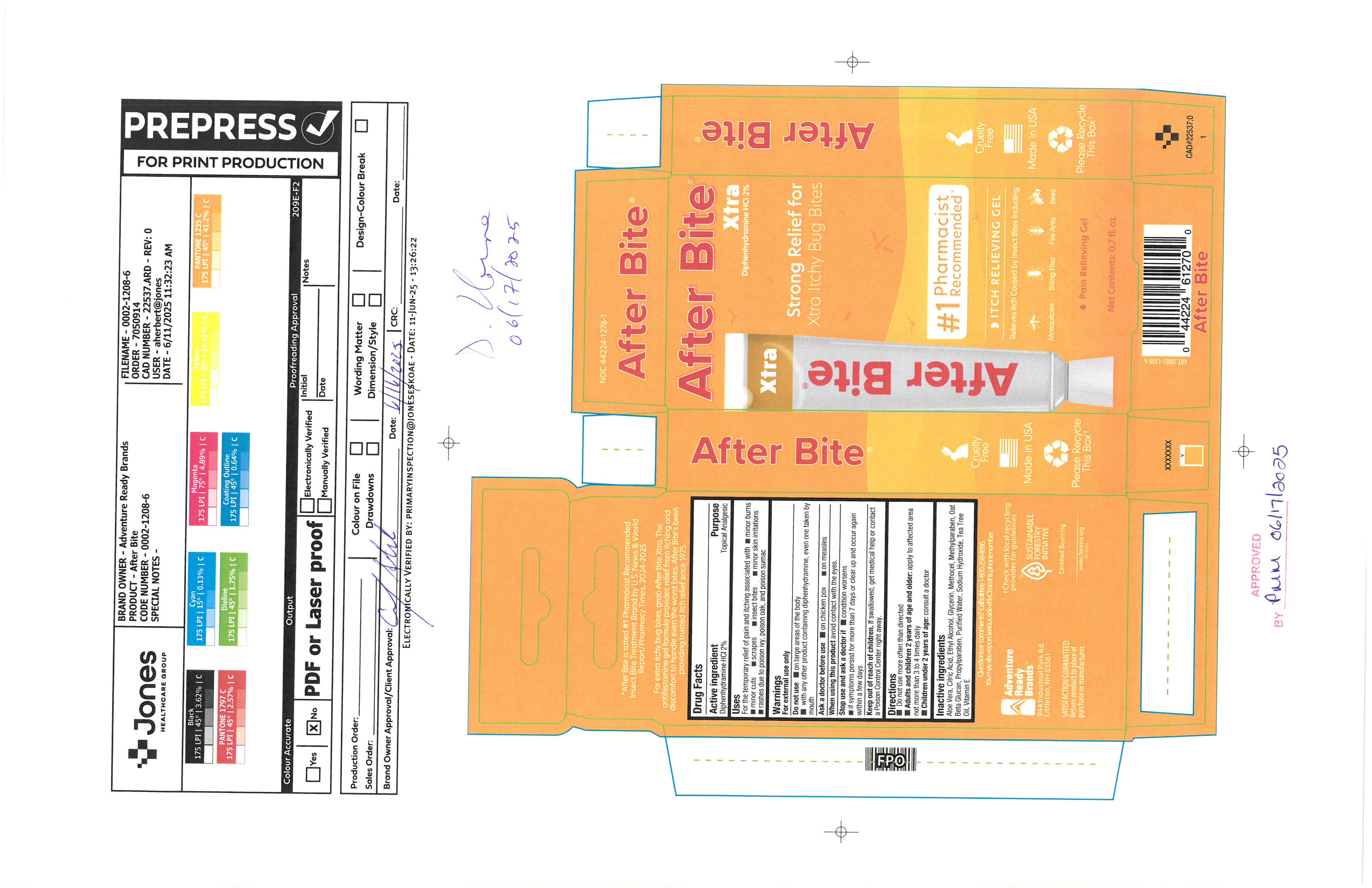 DRUG LABEL: After Bite Xtra
NDC: 44224-1276 | Form: GEL
Manufacturer: Tender Corporation d/b/a Adventure Ready Brands
Category: otc | Type: HUMAN OTC DRUG LABEL
Date: 20251001

ACTIVE INGREDIENTS: DIPHENHYDRAMINE HYDROCHLORIDE 0.4 g/20 g
INACTIVE INGREDIENTS: WATER 12.12 g/20 g; METHYLPARABEN 0.04 g/20 g; ANHYDROUS CITRIC ACID 0.044 g/20 g; PROPYLPARABEN 0.02 g/20 g; ALCOHOL 5.2 g/20 g; GLYCERIN 0.8 g/20 g; ALOE VERA LEAF 0.82 g/20 g; .ALPHA.-TOCOPHEROL ACETATE 0.06 g/20 g; TEA TREE OIL 0.1 g/20 g; SODIUM HYDROXIDE 0.26 g/20 g; HYPROMELLOSE, UNSPECIFIED 0.4 g/20 g; OAT 0.2 g/20 g

After Bite Xtra

Active Ingredients

Diphenhydramine HCl 2%

Purpose

Topical Analgesic

Uses

For the temporary relief of pain and itching associated with minor burns minor cuts oscrapes insect bite minor skin irritations rashes due to poison ivy, poison oak, and poison sumac

Warnings

For External use only

Do Not Use

on large areas of the body with any other product containing diphenhydramine, even one taken by mouth

Ask a doctor before use

on chicken pox on measles

When using this product

avoid contact with eyes

Stop use and ask a doctor if

conditions worsens if symptoms persist for more than 7 days or clear up and occur again within a few days

Keep out of reach of children

if swollowed, get medical help or contact a poison control center right away.

Directions

Do not use more often than directed

Adults and children 2 years of age and older: apply to affected area not more than 3 to 4 times daily

Children under 2 years of age : consult a doctor

Inactive Ingredients

Aloe Vera, Ciric Acid, Ethyl Alcohol, Glycerin, Methocel, Methylparaben, Oat beta Glucan, Propylparaben, purified water, sodium hydroxide, tea tree oil, vitamin e

Dosage

Adults and children over 2 apply to affected are 3 to 4 times day not more